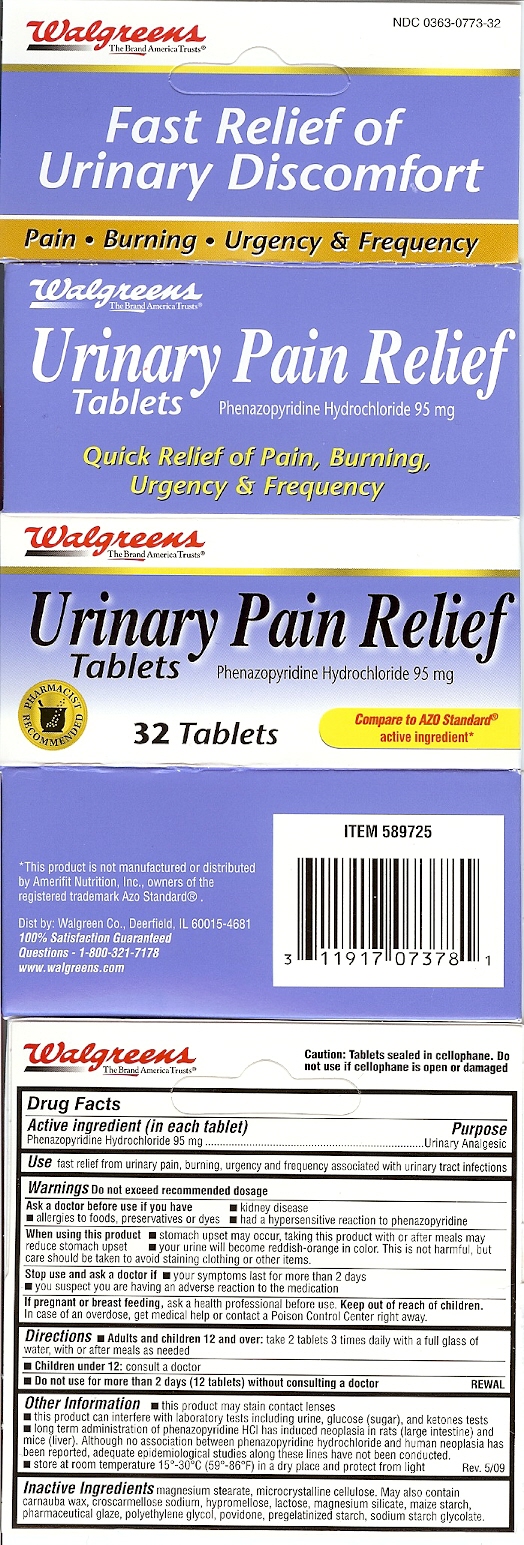 DRUG LABEL: Walgreens Urinary Pain Relief
NDC: 0363-0773 | Form: TABLET
Manufacturer: Walgreens Co
Category: otc | Type: HUMAN OTC DRUG LABEL
Date: 20110126

ACTIVE INGREDIENTS: PHENAZOPYRIDINE HYDROCHLORIDE 95 mg/1 1
INACTIVE INGREDIENTS: MAGNESIUM STEARATE; CELLULOSE, MICROCRYSTALLINE; CARNAUBA WAX; CROSCARMELLOSE SODIUM; HYPROMELLOSES ; LACTOSE; MAGNESIUM SILICATE

DRUG FACTS

ACTIVE INGREDIENT

Phenazopyridine Hydrochloride 95 mg

Purpose;
Urinary Analgesic

Uses
fast relief from urinary pain,burning,urgency and frequency associated with
urinary tract infections.

WARNINGS

Do not exceed recommended dosage

Ask a Doctor before use if you have
kidney disease,
allergies to foods,preservatives or dyes,
had a hypersensitive reaction to phenazopyridine.

When using this product
stomach upset may occur,taking this product with or after meals may
reduce stomach upset,
your urine will become reddish orange in color.This is not harmful,but care should
be taken to avoid staining clothing or other items.

Stop use and ask a doctor if
if your symptoms last for more than 2 days
you suspect you are having an adverse reaction
to the medication.

PREGNANCY OR BREAST FEEDING

If pregnant or breast feeding, ask a health professional before use.

Keep out of reach of children
in case of an overdose,get medical help or contact
a Poison Control Center right away.

Directions
Adults and children 12 and over; take 2 tablets 3 times daily with a
full glass of water,with or after meals as needed.
Children under 12 consult a doctor.
Do not use for more than 2 days ;12 tablets; without consulting a doctor.

INACTIVE INGREDIENT

magnesium stearate,microcrystalline cellulose.May also contain carnauba wax,
croscarmellose sodium,hypromellose,lactose,magnesium silicate,maize starch,pharmaceutical
glaze,polyethylene glycol,povidone,pregelatinized starch,sodium starch glycolate.